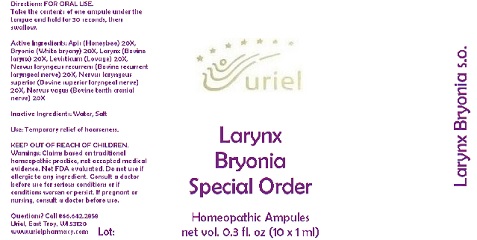 DRUG LABEL: Larynx Bryonia Special Order
NDC: 48951-6015 | Form: LIQUID
Manufacturer: Uriel Pharmacy Inc.
Category: homeopathic | Type: HUMAN OTC DRUG LABEL
Date: 20180530

ACTIVE INGREDIENTS: APIS MELLIFERA 20 [hp_X]/1 mL; BRYONIA ALBA ROOT 20 [hp_X]/1 mL; THYROID, BOVINE 20 [hp_X]/1 mL; LEVISTICUM OFFICINALE ROOT 20 [hp_X]/1 mL; BOS TAURUS NERVE 20 [hp_X]/1 mL
INACTIVE INGREDIENTS: WATER; SODIUM CHLORIDE

Larynx Bryonia Special Order

INDICATIONS AND USAGE

Directions: FOR ORAL USE.

DOSAGE AND ADMINISTRATION

Take the contents of one ampule under the tongue and hold for 30 seconds, then swallow.

ACTIVE INGREDIENT

Active Ingredients: Apis (Honeybee) 20X, Bryonia (White bryony) 20X, Larynx (Bovine larynx) 20X, Levisticum (Lovage) 20X, Nervus laryngeus recurrens (Bovine recurrent laryngeal nerve) 20X, Nervus laryngeus superior (Bovine superior laryngeal nerve) 20X, Nervus vagus (Bovine tenth cranial nerve) 20X

Inactive Ingredients: Water, Salt

PURPOSE

Use: Temporary relief of hoarseness.

KEEP OUT OF REACH OF CHILDREN.

WARNINGS

Warnings: Claims based on traditional homeopathic practice, not accepted medical evidence. Not FDA evaluated. Do not use if allergic to any ingredient. Consult a doctor before use for serious conditions or if conditions worsen or persist. If pregnant or nursing, consult a doctor before use.

QUESTIONS

Questions? Call 866.642.2858 Uriel, East Troy, WI 53120 www.urielpharmacy.com